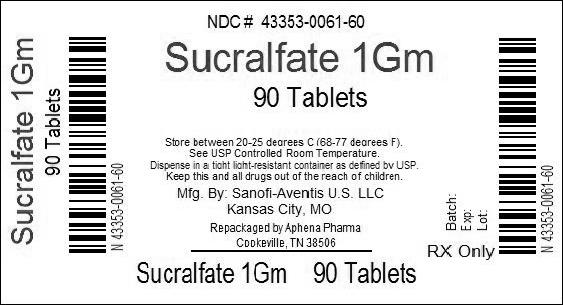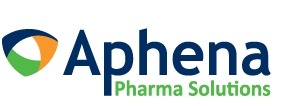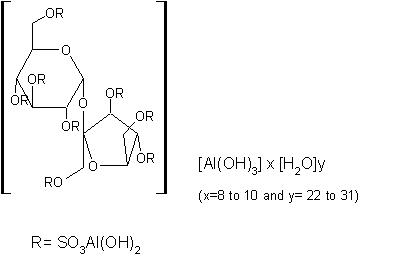 DRUG LABEL: Sucralfate
NDC: 43353-061 | Form: TABLET
Manufacturer: Aphena Pharma Solutions - Tennessee, LLC
Category: prescription | Type: HUMAN PRESCRIPTION DRUG LABEL
Date: 20140502

ACTIVE INGREDIENTS: SUCRALFATE 1 g/1 1
INACTIVE INGREDIENTS: MAGNESIUM STEARATE; CELLULOSE, MICROCRYSTALLINE; FD&C BLUE NO. 1; STARCH, CORN

Prescribing Information as of
June 2008A
SUCRALFATE
Tablets Rx only

DESCRIPTION

Sucralfate is an α-D-glucopyranoside, β-D-fructofuranosyl-, octakis-(hydrogen sulfate), aluminum complex.

Tablets for oral administration contain 1 g of sucralfate.
Also contain: FD&C Blue #1 Lake, magnesium stearate, microcrystalline cellulose, and starch.
Therapeutic category: antiulcer.

CLINICAL PHARMACOLOGY

Sucralfate is only minimally absorbed from the gastrointestinal tract. The small amounts of the sulfated disaccharide that are absorbed are excreted primarily in the urine.

Although the mechanism of sucralfate’s ability to accelerate healing of duodenal ulcers remains to be fully defined, it is known that it exerts its effect through a local, rather than systemic, action. The following observations also appear pertinent:

- Studies in human subjects and with animal models of ulcer disease have shown that sucralfate forms an ulcer-adherent complex with proteinaceous exudate at the ulcer site.
- In vitro, a sucralfate-albumin film provides a barrier to diffusion of hydrogen ions.
- In human subjects, sucralfate given in doses recommended for ulcer therapy inhibits pepsin activity in gastric juice by 32%.
- In vitro, sucralfate adsorbs bile salts.

These observations suggest that sucralfate’s antiulcer activity is the result of formation of an ulcer-adherent complex that covers the ulcer site and protects it against further attack by acid, pepsin, and bile salts. There are approximately 14-16 mEq of acid-neutralizing capacity per 1-g dose of sucralfate.

CLINICAL TRIALS

Acute Duodenal Ulcer

Over 600 patients have participated in well-controlled clinical trials worldwide. Multicenter trials conducted in the United States, both of them placebo-controlled studies with endoscopic evaluation at 2 and 4 weeks,showed:

STUDY 1
Treatment Groups | Ulcer Healing/ No. Patients
Treatment Groups | 2 wk | 4 wk (Overall)
Sucralfate | 37/105 (35.2%) | 82/109 (75.2%)
Placebo | 26/106 (24.5%) | 68/107 (63.6%)

STUDY 2
Treatment Groups | Ulcer Healing/ No. Patients
Treatment Groups | 2 wk | 4 wk (Overall)
Sucralfate | 8/24 (33%) | 22/24 (92%)
Placebo | 4/31 (13%) | 18/31 (58%)

The sucralfate-placebo differences were statistically significant in both studies at 4 weeks but not at 2 weeks. The poorer result in the first study may have occurred because sucralfate was given 2 hours after meals and at bedtime rather than 1 hour before meals and at bedtime, the regimen used in international studies and in the second United States study. In addition, in the first study liquid antacid was utilized as needed, whereas in the second study antacid tablets were used.

Maintenance Therapy After Healing of Duodenal Ulcer

Two double-blind randomized placebo-controlled U.S. multicenter trials have demonstrated that sucralfate (1 g bid) is effective as maintenance therapy following healing of duodenal ulcers.

In one study, endoscopies were performed monthly for 4 months. Of the 254 patients who enrolled, 239 were analyzed in the intention-to-treat life table analysis presented below.

Duodenal Ulcer Recurrence Rate (%)
Drug | Months of Therapy
Drug | n | 1 | 2 | 3 | 4
Sucralfate | 122 | 20 [P<0.05] | 30 | 38 [P<0.01] | 42
Placebo | 117 | 33 | 46 | 55 | 63

In this study, prn antacids were not permitted.

In the other study, scheduled endoscopies were performed at 6 and 12 months, but for-cause endoscopies were permitted as symptoms dictated. Median symptom scores between the sucralfate and placebo groups were not significantly different. A life table intention-to-treat analysis for the 94 patients enrolled in the trial had the following results:

Duodenal Ulcer Recurrence Rate (%)
Drug | n | 6 Months | 12 Months
Sucralfate | 48 | 19 [P<0.002] | 27
Placebo | 46 | 54 | 65

In this study, prn antacids were permitted.

Data from placebo-controlled studies longer than 1 year are not available.

INDICATIONS AND USAGE

Sucralfate is indicated in:

- Short-term treatment (up to 8 weeks) of active duodenal ulcer. While healing with sucralfate may occur during the first week or two, treatment should be continued for 4 to 8 weeks unless healing has been demonstrated by x-ray or endoscopic examination.

- Maintenance therapy for duodenal ulcer patients at reduced dosage after healing of acute ulcers.

CONTRAINDICATIONS

There are no known contraindications to the use of sucralfate.

PRECAUTIONS

Duodenal ulcer is a chronic, recurrent disease. While short-term treatment with sucralfate can result in complete healing of the ulcer, a successful course of treatment with sucralfate should not be expected to alter the posthealing frequency or severity of duodenal ulceration.

Special Populations: Chronic Renal Failure and Dialysis Patients

When sucralfate is administered orally, small amounts of aluminum are absorbed from the gastrointestinal tract. Concomitant use of sucralfate with other products that contain aluminum, such as aluminum-containing antacids, may increase the total body burden of aluminum. Patients with normal renal function receiving the recommended doses of sucralfate and aluminum-containing products adequately excrete aluminum in the urine. Patients with chronic renal failure or those receiving dialysis have impaired excretion of absorbed aluminum. In addition, aluminum does not cross dialysis membranes because it is bound to albumin and transferrin plasma proteins. Aluminum accumulation and toxicity (aluminum osteodystrophy, osteomalacia, encephalopathy) have been described in patients with renal impairment. Sucralfate should be used with caution in patients with chronic renal failure.

Drug Interactions

Some studies have shown that simultaneous sucralfate administration in healthy volunteers reduced the extent of absorption (bioavailability) of single doses of the following: cimetidine, digoxin, fluoroquinolone antibiotics, ketoconazole, l-thyroxine, phenytoin, quinidine, ranitidine, tetracycline, and theophylline. Subtherapeutic prothrombin times with concomitant warfarin and sucralfate therapy have been reported in spontaneous and published case reports. However, two clinical studies have demonstrated no change in either serum warfarin concentration or prothrombin time with the addition of sucralfate to chronic warfarin therapy.

The mechanism of these interactions appears to be nonsystemic in nature, presumably resulting from sucralfate binding to the concomitant agent in the gastrointestinal tract. In all cases studied to date (cimetidine, ciprofloxacin, digoxin, norfloxacin, ofloxacin, and ranitidine), dosing the concomitant medication 2 hours before sucralfate eliminated the interaction. Because of the potential of sucralfate to alter the absorption of some drugs, sucralfate should be administered separately from other drugs when alterations in bioavailability are felt to be critical. In these cases, patients should be monitored appropriately.

Carcinogenesis, Mutagenesis, Impairment of Fertility

Chronic oral toxicity studies of 24 months’ duration were conducted in mice and rats at doses up to 1 g/kg (12 times the human dose).

There was no evidence of drug-related tumorigenicity. A reproduction study in rats at doses up to 38 times the human dose did not reveal any indication of fertility impairment. Mutagenicity studies were not conducted.

Pregnancy

Teratogenic effects. Pregnancy Category B.

Teratogenicity studies have been performed in mice, rats, and rabbits at doses up to 50 times the human dose and have revealed no evidence of harm to the fetus due to sucralfate. There are, however, no adequate and well-controlled studies in pregnant women. Because animal reproduction studies are not always predictive of human response, this drug should be used during pregnancy only if clearly needed.

Nursing Mothers

It is not known whether this drug is excreted in human milk. Because many drugs are excreted in human milk, caution should be exercised when sucralfate is administered to a nursing woman.

Pediatric Use

Safety and effectiveness in pediatric patients have not been established.

ADVERSE REACTIONS

Adverse reactions to sucralfate in clinical trials were minor and only rarely led to discontinuation of the drug. In studies involving over 2700 patients treated with sucralfate tablets, adverse effects were reported in 129 (4.7%).

Constipation was the most frequent complaint (2%). Other adverse effects reported in less than 0.5% of the patients are listed below by body system:

Gastrointestinal: diarrhea, nausea, vomiting, gastric discomfort, indigestion, flatulence, dry mouth

Dermatological: pruritus, rash

Nervous System: dizziness, insomnia, sleepiness, vertigo

Other: back pain, headache

Postmarketing reports of hypersensitivity reactions, including urticaria (hives), angioedema, respiratory difficulty, rhinitis, laryngospasm, and facial swelling have been reported in patients receiving sucralfate tablets. Similar events were reported with sucralfate suspension. However, a causal relationship has not been established.

Bezoars have been reported in patients treated with sucralfate. The majority of patients had underlying medical conditions that may predispose to bezoar formation (such as delayed gastric emptying) or were receiving concomitant enteral tube feedings.

Inadvertent injection of insoluble sucralfate and its insoluble excipients has led to fatal complications, including pulmonary and cerebral emboli. Sucralfate is not intended for intravenous administration.

OVERDOSAGE

Due to limited experience in humans with overdosage of sucralfate, no specific treatment recommendations can be given. Acute oral toxicity studies in animals, however, using doses up to 12 g/kg body weight, could not find a lethal dose. Sucralfate is only minimally absorbed from the gastrointestinal tract. Risks associated with acute overdosage should, therefore, be minimal. In rare reports describing sucralfate overdose, most patients remained asymptomatic. Those few reports where adverse events were described included symptoms of dyspepsia, abdominal pain, nausea, and vomiting.

DOSAGE AND ADMINISTRATION

Active Duodenal Ulcer. The recommended adult oral dosage for duodenal ulcer is 1 g four times a day on an empty stomach.

Antacids may be prescribed as needed for relief of pain but should not be taken within one-half hour before or after sucralfate.

While healing with sucralfate may occur during the first week or two, treatment should be continued for 4 to 8 weeks unless healing has been demonstrated by x-ray or endoscopic examination.

Maintenance Therapy. The recommended adult oral dosage is 1 g twice a day.

HOW SUPPLIED

Repackaged by Aphena Pharma Solutions - TN.
See Repackaging Information for available configurations.

Sucralfate 1-g tablets are supplied in bottles of 90, 100, 360 and 500.
Light blue, scored, oblong tablets are engraved WATSON 780 on one side and are blank with bisect on the other.
Prescribing Information as of June 2008A

Manufactured for:
Watson Laboratories, Inc.
Corona, CA 92880 USA
Manufactured by:
sanofi-aventis U.S. LLC
Kansas City, MO 64137 USA

50088983

Repackaging Information

Please reference the How Supplied section listed above for a description of individual tablets or capsules. This drug product has been received by Aphena Pharma - TN in a manufacturer or distributor packaged configuration and repackaged in full compliance with all applicable cGMP regulations. The package configurations available from Aphena are listed below:

Count | 1Gm
90 | 43353-061-60
120 | 43353-061-70
360 | 43353-061-94

Store between 20°-25°C (68°-77°F). See USP Controlled Room Temperature. Dispense in a tight light-resistant container as defined by USP. Keep this and all drugs out of the reach of children.

Repackaged by:
Cookeville, TN 38506
20140502SC

PRINCIPAL DISPLAY PANEL - 1Gm

NDC 43353-061 - Sucralfate 1Gm - Rx Only